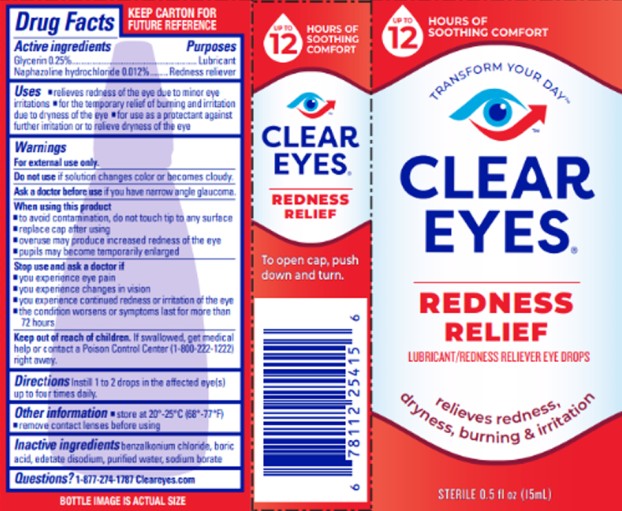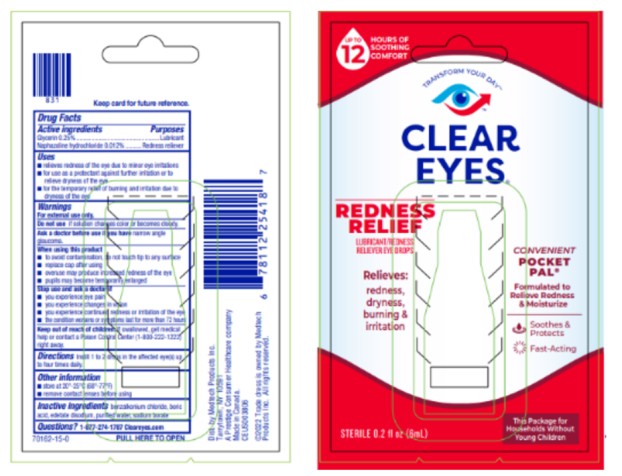 DRUG LABEL: Clear Eyes Redness Relief
NDC: 67172-797 | Form: LIQUID
Manufacturer: Prestige Brands Holdings, Inc.
Category: otc | Type: HUMAN OTC DRUG LABEL
Date: 20250429

ACTIVE INGREDIENTS: NAPHAZOLINE HYDROCHLORIDE 0.12 mg/1 mL; GLYCERIN 2.5 mg/1 mL
INACTIVE INGREDIENTS: BENZALKONIUM CHLORIDE; BORIC ACID; EDETATE DISODIUM; WATER; SODIUM BORATE

Clear Eyes Redness Relief

Clear Eyes Redness Relief

Drug Facts

Active Ingredients

Glycerin 0.25%

Purpose

Lubricant

Active Ingredients

Naphazoline hydrochloride 0.012%

Purpose

Redness Reliever

Uses

- relieves redness of the eye due to minor eye irritations
- for the temporary relief of burning and irritation due to dryness of the eye
- for use as a protectant against further irritation or to relieve dryness of the eye

Warnings

For external use only.

Do not use

if solution changes color or becomes cloudy.

Ask a doctor before use

if you have narrow angle glaucoma.

When using this product

- to avoid contamination, do not touch tip to any surface
- replace cap after using
- overuse may produce increased redness of the eye
- pupils may become temporarily enlarged

Stop use and ask a doctor if

- you experience eye pain
- you experience changes in vision
- you experience continued redness or irritation of the eye
- the condition worsens or symptoms last for more than 72 hours

Keep out of reach of children.

If swallowed, get medical help or contact a Poison Control Center (1-800-222-1222) right away.

Directions

Instill 1 to 2 drops in the affected eye(s) up to four times daily.

Other Information

- store at 20°-25°C (68°-77°F)
- remove contact lenses before using

Inactive Ingredients

benzalkonium chloride, boric acid, edetate disodium, purified water, sodium borate

Questions?

1-877-274-1787 Cleareyes.com.

Clear Eyes Redness Relief, Handy Pocket Pal

Drug Facts

Active Ingredients

Glycerin 0.25%

Purpose

Lubricant

Active Ingredients

Naphazoline hydrochloride 0.012%

Purpose

Redness Reliever

Uses

- relieves redness of the eye due to minor eye irritations
- for use as a protectant against further irritation or to relieve dryness of the eye for the temporary relief of burning and irritation due to dryness of the eye

Warnings

For external use only.

Do not use

if solution changes color or becomes cloudy.

Ask a doctor before use if you have

narrow angle glaucoma.

When using this product

- to avoid contamination, do not touch tip to any surface
- replace cap after using
- overuse may produce increased redness of the eye
- pupils may become temporarily enlarged

Stop use & ask a doctor if

- you experience eye pain
- you experience changes in vision
- you experience continued redness or irritation of the eye
- the condition worsens or symptoms last for more than 72 hours

Keep out of reach of children.

If swallowed, get medical help or contact a Poison Control Center (1-800-222-1222) right away.

Directions

Instill 1 to 2 drops in the affected eye(s) up to four times daily.

Other Information

- store at 20° -25°C (68° -77°F)
- remove contact lenses before using

Inactive Ingredients

benzalkonium chloride, boric acid, edetate disodium, purified water, sodium borate

Questions?

1-877-274-1787 cleareyes.com

PRINCIPAL DISPLAY PANEL

CLEAR EYES ®
REDNESS RELIEF
LUBRICANT/REDNESS RELIEVER EYE DROPS
STERILE 0.5 FL OZ (15 mL)

PRINCIPAL DISPLAY PANEL

CLEAR EYES ®
REDNESS RELIEF
LUBRICANT/REDNESS RELIEVER EYE DROPS
POCKET PAL®
STERILE 0.2 FL OZ (6 mL)